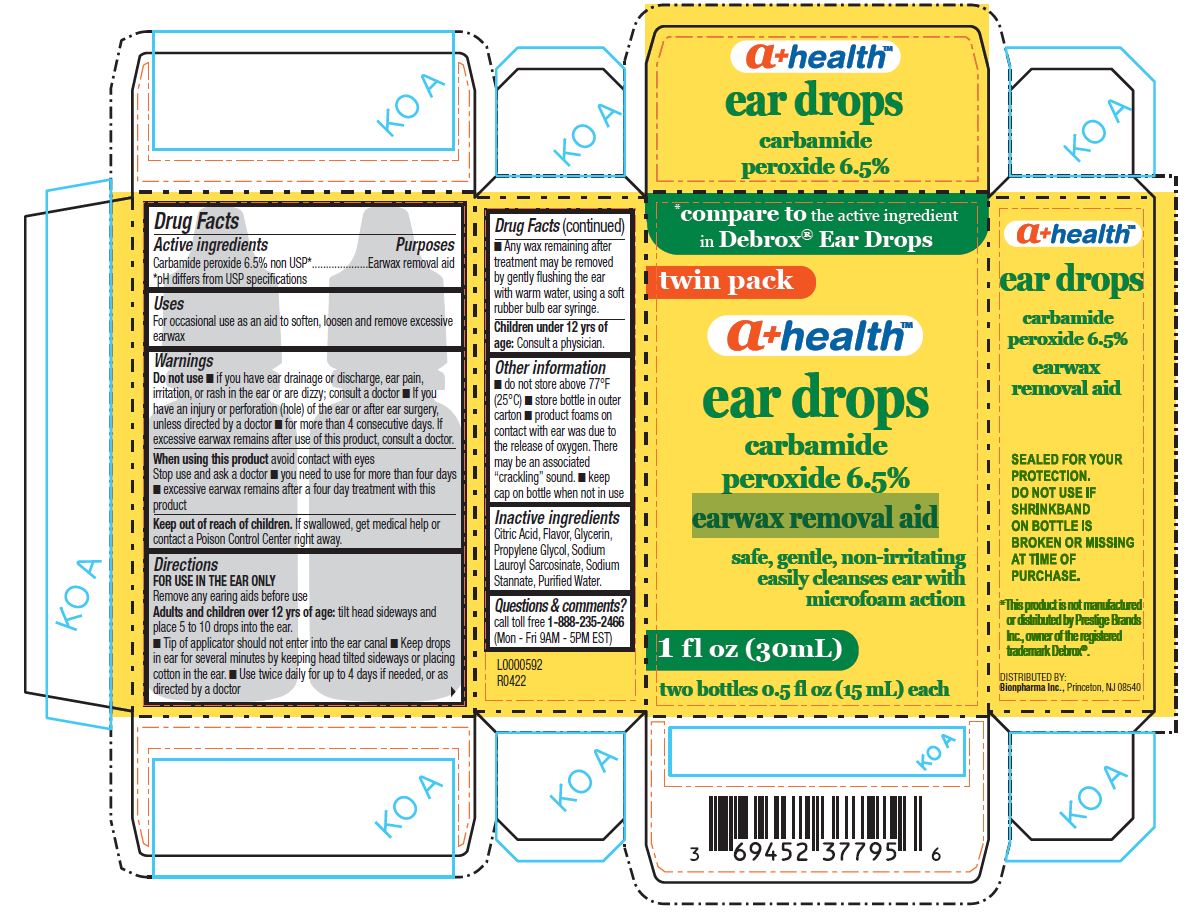 DRUG LABEL: ear drops
NDC: 69452-377 | Form: LIQUID
Manufacturer: Bionpharma Inc.
Category: otc | Type: HUMAN OTC DRUG LABEL
Date: 20241223

ACTIVE INGREDIENTS: CARBAMIDE PEROXIDE 0.065 mg/1 mL
INACTIVE INGREDIENTS: ANHYDROUS CITRIC ACID; SODIUM STANNATE; SODIUM LAUROYL SARCOSINATE; PROPYLENE GLYCOL; WATER; GLYCERIN

ear drops

Active ingredients

Carbamide Peroxide 6.5% non USP*

*pH differs from USP specifications

Purposes

Earwax removal aid

Uses

For occasional use as an aid to soften, loosen and remove excessive earwax

Warnings

Do not use

- if you have ear drainage or discharge, ear pain, irritation, or rash in the ear or are dizzy; consult a doctor
- If you have an injury or perforation (hole) of the ear or after ear surgery, unless directed by a doctor
- for more than 4 consecutive days. If excessive earwax remains after use of this product, consult a doctor.

When using this product

avoid contact with eyes
Stop use and ask a doctor

- you need to use for more than four days
- excessive earwax remains after a four day treatment with this product

KEEP OUT OF REACH OF CHILDREN

Keep this and all drugs out of the reach of children. If swallowed, get medical help or contact a Poison Control Center right away.

Directions

FOR USE IN THE EAR ONLY
Remove any earing aids before use

Adults and children over 12 yrs of age: tilt head to the side and place 10 drops into the ear.

- Tip of applicator should not enter into the ear canal
- Keep drops in ear for several minutes by keeping head tilted sideways or placing cotton in the ear.
- Use twice daily for up to 4 days if needed, or as directed by a doctor.
- Any wax remaining after treatment may be removed by gently flushing the ear with warm water, using a soft rubber bulb ear syringe.

Children under 12 yrs of age: Consult a physician.

Other information

- do not store above 77°F (25°C)
- store bottle in outer carton
- product foams on contact with ear was due to the release of oxygen. There may be an associated “crackling” sound.
- keep cap on bottle when not in use

Inactive ingredients

Citric Acid, Flavor, Glycerin, Propylene Glycol, Sodium Lauroyl Sarcosinate, Sodium Stannate, Purified Water.

Questions & comments?

call toll free 1-888-235-2466
(Mon - Fri 9AM - 5PM EST)

a+health™

ear drops
carbamide
peroxide 6.5%

earwax
removal aid

SEALED FOR YOUR

PROTECTION.

DO NOT USE IF

SHRINKBAND

ON BOTTLE IS

BROKEN OR MISSING

AT TIME OF

PURCHASE.

*This product is not manufactured
or distributed by Prestige Brands
Inc., owner of the registered
trademark Debrox®.

DISTRIBUTED BY:
Bionpharma Inc., Princeton, NJ 08540

L0000592

R0422

Carton labeling

*compare to the active ingredient
in Debrox® Ear Drops

twin pack

a+health™

ear drops
carbamide
peroxide 6.5%

earwax removal aid

safe, gentle, non-irritating
easily cleanses ear with
microfoam action

1 fl oz (30mL)
two bottles 0.5 fl oz (15 mL) each